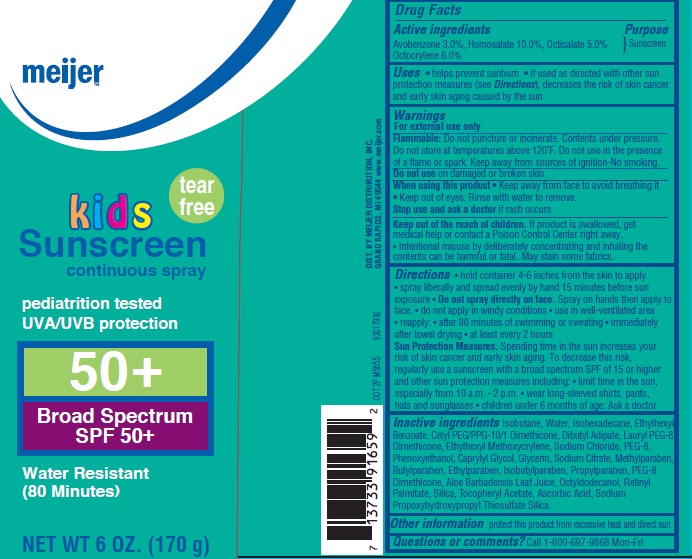 DRUG LABEL: Meijer Kids Tear Free SPF 50
NDC: 41250-928 | Form: SPRAY
Manufacturer: Meijer Distribution, Inc.
Category: otc | Type: HUMAN OTC DRUG LABEL
Date: 20160311

ACTIVE INGREDIENTS: AVOBENZONE 3 g/100 g; HOMOSALATE 10 g/100 g; OCTISALATE 5 g/100 g; OCTOCRYLENE  6 g/100 g
INACTIVE INGREDIENTS: ISOBUTANE; WATER; ISOHEXADECANE; 2-ETHYLHEXYL BENZOATE; DIBUTYL ADIPATE; ETHYLHEXYL METHOXYCRYLENE ; SODIUM CHLORIDE; POLYETHYLENE GLYCOL 400; CAPRYLYL GLYCOL; GLYCERIN; SODIUM CITRATE, UNSPECIFIED FORM; PEG-8 DIMETHICONE; ALOE VERA LEAF; OCTYLDODECANOL; VITAMIN A PALMITATE; SILICON DIOXIDE; .ALPHA.-TOCOPHEROL ACETATE; ASCORBIC ACID; SODIUM PROPOXYHYDROXYPROPYL THIOSULFATE SILICA; PHENOXYETHANOL; METHYLPARABEN; BUTYLPARABEN; ETHYLPARABEN; ISOBUTYLPARABEN; PROPYLPARABEN

Drug Facts

Active ingredients

Avobenzone 3.0%, Homosalate 10.0%, Octisalate 5.0%, Octocrylene 6.0%

Purpose

Sunscreen

Uses

• helps prevent sunburn

• if used as directed with other sun protection measures (see Directions), decreases the risk of skin cancer and early skin aging caused by the sun

Warnings

For external use only

Flammable: Do not puncture or incinerate. Contents under pressure. Do not store at temperature above 120^0F. Do not use in the presence of a flame or spark. Keep away from sources of ignition - No smoking.

Do not use

on damaged or broken skin

When using this product

- Keep away from face to avoid breathing it.
- Keep out of eyes. Rinse with water to remove.

Stop use and ask a doctor

if rash occurs

Keep out of reach of children.

- If product is swallowed, get medical help or contact a Poison Control center right away.

- Intentional misuse by deliberately concentrating and inhaling the contents can be harmful or fatal.
- May stain some fabrics.

Directions

- hold container 4-6 inches from the skin to apply
- spray liberally and spread evenly by hand 15 minutes before sun exposure
- Do not spray directly on face. Spray on hands then apply to face.
- do not apply in windy conditions
- use in well-ventilated area
- reapply:
- after 80 minutes of swimming or sweating
- immediately after towel drying
- at least every 2 hours
- Sun Protection Measures. Spending time in the sun increases your risk of skin cancer and early skin aging. To decrease this risk, regularly use a sunscreen with a broad spectrum SPF of 15 or higher and other sun production measures including:
- limit time in the sun, especially from 10 a.m. to 2 p.m.
- wear long-sleeved shirts, pants, hats, and sunglasses
- children under 6 months of age: Ask a Doctor

Inactive ingredients

Isobutane, Water, Isohexadecane, Ethylhexyl Benzoate, Cetyl PEG/PPG-10/1 Dimethicone, Dibutyl Adipate, Lauryl PEG-8 Dimethicone, Ethylhexyl Methoxycrylene, Sodium Chloride, PEG-8, Caprylyl Glycol, Glycerin, Sodium Citrate, PEG-8 Dimethicone, Aloe Barbadensis Leaf Juice, Octyldodecanol, Retinyl Palmitate, Silica, Tocopheryl Acetate, Ascorbic Acid, Sodium Propoxyhydroxypropyl Thiosulfate Silica, Phenoxyethanol, Methylparaben, Butylparaben, Ethylparaben, Isobutylparaben, Propylparaben.

Other information

protect this product from excessing heat and direct sun

Questions or comments?

Call 1-800-697-9868 Mon-Fri

Principal Display Panel

NDC: 41250-928-55

meijer

tear free

Kids Sunscreen

continuous spray

pediatrician tested

UVA/UVB protection

50+

Broad Spectrum

SPF 50+

Water Resistant

(80 minutes)

NET WT 6 OZ. (170 g)